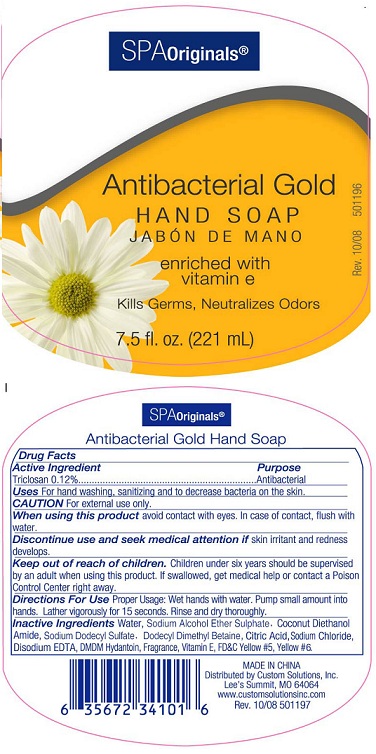 DRUG LABEL: Spa Originals Antibacterial Gold Hand
NDC: 76405-011 | Form: SOAP
Manufacturer: Custom Solutions, Inc
Category: otc | Type: HUMAN OTC DRUG LABEL
Date: 20110927

ACTIVE INGREDIENTS: TRICLOSAN 0.12 mL/100 mL
INACTIVE INGREDIENTS: WATER; COCO DIETHANOLAMIDE; SODIUM LAURYL SULFATE; CITRIC ACID MONOHYDRATE; SODIUM CHLORIDE; EDETATE DISODIUM; DMDM HYDANTOIN; ALPHA-TOCOPHEROL; FD&C YELLOW NO. 5; FD&C YELLOW NO. 6

Spa Originals Antibacterial Gold Hand Soap

Active Ingredient

Triclosan 0.12%

Purpose

Antibacterial

Uses

For hand washing, sanitizing and to decrease bacteria on the skin

Caution

For external use only.

When using this product

avoid contact with the eyes

Discontinue use and seek medical attention if

skin irritant and redness develops

Keep out of reach of children

Children under six years should be supervised by an adult when using this product. If swallowed, get medical help or contact a Poison Control Center right away.

Directions for use

Proper usage: Wet hands with water. Pump small amount into hands. Lather vigorously for 15 seconds. Rinse and dry thoroghly.

Inactive Ingredients

Water, Sodium Alcohol Ether Sulphate, Coconut Diethanolamide, Sodium Dodecyl Sulfate, Dodecyl Dimethyl Betaine, Citric Acid, Sodium Cloride, Disodium EDTA, DMDM Hydantoin, Fragrance, Vitamin E, FDandC Yellow 5, Yellow 6

MADE IN CHINA
Distrubuted by Custom Solutions, Inc.
Lee's Summit, MO 64064
www.customsolutionsinc.com

PACKAGE LABEL

Spa Originals

Antibacterial Gold

HAND SOAP

enriched with vitamin e

Kills Germs, Neutralizes Odors

7.5 fl. oz. (221mL)